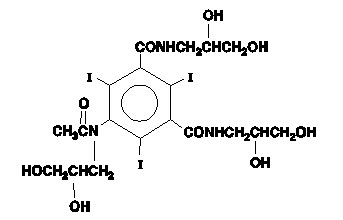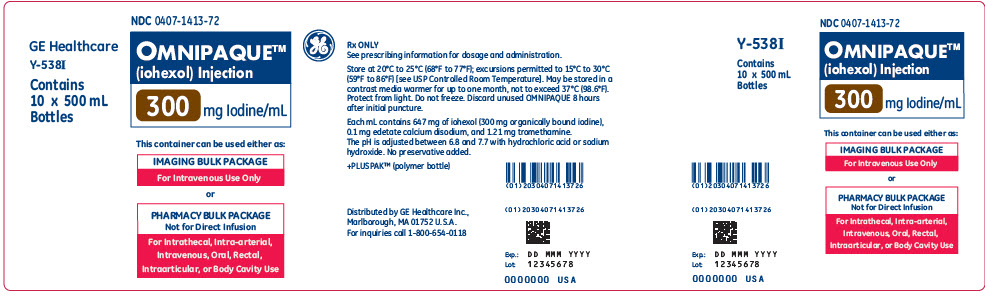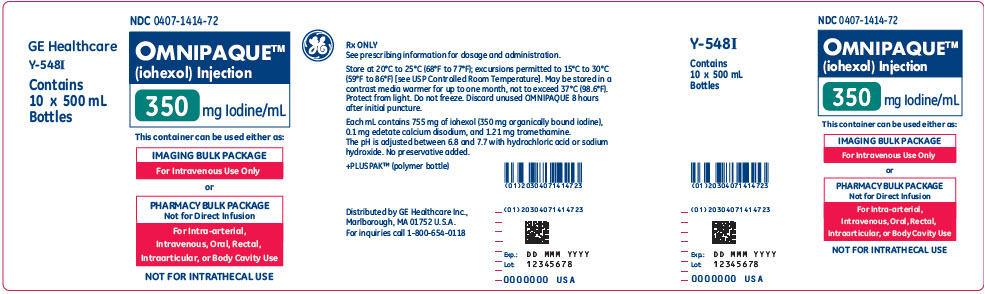 DRUG LABEL: Omnipaque
NDC: 0407-1413 | Form: INJECTION, SOLUTION
Manufacturer: GE Healthcare
Category: prescription | Type: HUMAN PRESCRIPTION DRUG LABEL
Date: 20241018

ACTIVE INGREDIENTS: Iohexol 300 mg/1 mL
INACTIVE INGREDIENTS: tromethamine 1.21 mg/1 mL; edetate calcium disodium 0.1 mg/1 mL; hydrochloric acid; sodium hydroxide

HIGHLIGHTS OF PRESCRIBING INFORMATION

These highlights do not include all the information needed to use OMNIPAQUE safely and effectively. See full prescribing information for OMNIPAQUE.
OMNIPAQUE (iohexol) injection, for intrathecal, intra-arterial, intravenous, oral, rectal, intraarticular, or body cavity use
OMNIPAQUE (iohexol) oral solution
Initial U.S. Approval: 1985

WARNING: RISKS ASSOCIATED WITH INTRATHECAL ADMINISTRATION OF OMNIPAQUE INJECTION 140 mg IODINE/mL and 350 mg IODINE/mL

WARNING: RISKS ASSOCIATED WITH INTRATHECAL ADMINISTRATION OF OMNIPAQUE INJECTION 140 and 350 mg IODINE/mL

Use only the iodine concentrations and presentations recommended for intrathecal procedures. Intrathecal administration of a wrong iodine concentration, even if inadvertent, may cause death, convulsions, seizures, cerebral hemorrhage, coma, paralysis, arachnoiditis, acute renal failure, cardiac arrest, rhabdomyolysis, hyperthermia, and brain edema. (2.2, 2.8, 5.1)

RECENT MAJOR CHANGES

Indications and Usage, CT cerebral ventriculography (1.1) - Removed | 10/2024
Dosage and Administration (2.6, 2.10, 2.11) | 10/2024

1 INDICATIONS AND USAGE

OMNIPAQUE is a radiographic contrast agent indicated for intrathecal, intra-arterial, intravenous, oral, rectal, intraarticular, and body cavity imaging procedures in adults and pediatric patients. (1)

2 DOSAGE AND ADMINISTRATION

- For each imaging procedure, specific dosage forms, concentrations, and presentations are recommended.
- Individualize the concentration and volume according to the specific dosing tables and accounting for factors such as age, body weight, and condition of the patient, and the equipment and imaging technique used. (2.2, 2.3, 2.4, 2.5, 2.6, 2.7, 2.8, 2.9)
- See full prescribing information for complete dosing and administration information. (2)

3 DOSAGE FORMS AND STRENGTHS

- Injection: 140 mg iodine/mL, 180 mg iodine/mL, and 240 mg iodine/mL in single-dose vials/bottles; 300 mg iodine/mL and 350 mg iodine/mL in single-dose vials/bottles and imaging or pharmacy bulk package
- Oral Solution: 9 mg iodine/mL and 12 mg iodine/mL (3)

4 CONTRAINDICATIONS

- Hysterosalpingography during pregnancy (or suspected pregnancy), menstruation (or when menstruation is imminent), within 6 months after termination of pregnancy, within 30 days after conization or curettage, when signs of infection are present in any portion of the genital tract, including the external genitalia, and when reproductive tract neoplasia is known or suspected. (4)

5 WARNINGS AND PRECAUTIONS

- Hypersensitivity Reactions: Life-threatening or fatal reactions can occur. Always have emergency equipment and trained personnel available. (5.3)
- Acute Kidney Injury: Acute injury including renal failure can occur. Minimize dose and maintain adequate hydration to minimize risk. (5.4)
- Cardiovascular Adverse Reactions: Hemodynamic disturbances including shock and cardiac arrest may occur during or after administration. (5.5)
- Thyroid Dysfunction in Pediatric Patients 0 to 3 Years of Age: Individualize thyroid function monitoring based on risk factors such as prematurity. (5.9)

6 ADVERSE REACTIONS

Most common adverse reactions (incidence ≥ 1%) in adult patients

- Intrathecal: Headaches, pain including backache, neckache, stiffness and neuralgia, nausea, vomiting, dizziness
- Intra-arterial or intravenous: Pain, vision abnormalities (including blurred vision and photomas), headache, taste perversion, arrhythmias including premature ventricular contractions (PVCs) and premature atrial contractions (PACs), angina/chest pain, nausea
- Oral: Diarrhea, nausea, vomiting, abdominal pain, flatulence, headache
- Body Cavity: Pain, swelling, heat sensation (6.1)

To report SUSPECTED ADVERSE REACTIONS, contact GE Healthcare at 1-800-654-0118 or FDA at 1-800-FDA-1088 or www.fda.gov/medwatch.

8 USE IN SPECIFIC POPULATIONS

- Lactation: A lactating woman may pump and discard breast milk for 10 hours after OMNIPAQUE administration. (8.2)

FULL PRESCRIBING INFORMATION

WARNING: RISKS ASSOCIATED WITH INTRATHECAL ADMINISTRATION OF OMNIPAQUE INJECTION 140 mg IODINE/mL and 350 mg IODINE/mL

Use only the OMNIPAQUE iodine concentrations and presentations recommended for intrathecal procedure [see Dosage and Administration (2.2, 2.8)]. Intrathecal administration of OMNIPAQUE of a wrong iodine concentration, even if inadvertent, may cause death, convulsions, seizures, cerebral hemorrhage, coma, paralysis, arachnoiditis, acute renal failure, cardiac arrest, rhabdomyolysis, hyperthermia, and brain edema [see Warnings and Precautions (5.1)].

1 INDICATIONS AND USAGE

1.1 Intrathecal Procedures‡

OMNIPAQUE is indicated for:

- Myelography and computerized tomography (CT) myelography (lumbar, thoracic, cervical, total columnar) in adults and pediatric patients aged 2 weeks and older
- CT cisternography in adults and pediatric patients aged 2 weeks and older

1.2 Intra-arterial Procedures‡

OMNIPAQUE is indicated for:

- Cardiac ventriculography in adults and pediatric patients
- Aortography including studies of aorta and its branches in adults and pediatric patients
- Selective coronary arteriography in adults
- Cerebral arteriography in adults
- Peripheral arteriography in adults
- Intra-arterial digital subtraction angiography (IA-DSA) of the head, neck, abdominal, renal, and peripheral vessels in adults
- Pulmonary angiography in pediatric patients

1.3 Intravenous Procedures‡

OMNIPAQUE is indicated for:

- Excretory urography in adults and pediatric patients
- CT of the head and body in adults and pediatric patients
- Peripheral venography (phlebography) in adults
- Intravenous digital subtraction angiography (IV-DSA) of the head, neck, abdominal, renal, and peripheral vessels in adults

1.4 Oral or Rectal Procedures‡

OMNIPAQUE is indicated for:

- Radiographic examination of the gastrointestinal (GI) tract in adults and pediatric patients
- CT of the abdomen and pelvis in conjunction with intravenous administration of OMNIPAQUE in adults and pediatric patients

1.5 Intraarticular Procedures‡

OMNIPAQUE is indicated for:

- Arthrography in adults

1.6 Body Cavity Procedures‡

OMNIPAQUE is indicated for:

- Endoscopic retrograde pancreatography (ERP) and cholangiopancreatography (ERCP) in adults
- Herniography in adults
- Hysterosalpingography in adults
- Voiding cystourethrography (VCU) in pediatric patients

‡ Specific dosage forms, concentrations, and presentations of OMNIPAQUE are recommended for each type of imaging procedure [see Dosage and Administrations (2.2, 2.3, 2.4, 2.5, 2.6, 2.7, 2.8, 2.9) and Warnings and Precautions (5.1, 5.2)].

2 DOSAGE AND ADMINISTRATION

2.1 Important Dosage and Administration Instructions

- Specific dosage forms, concentrations, and presentations of OMNIPAQUE are recommended for each type of imaging procedure [see Dosage and Administration (2.2, 2.3, 2.4, 2.5, 2.6, 2.7, 2.8, 2.9) and Warnings and Precautions (5.1, 5.2)].
- Individualize the volume, strength, and rate of administration of OMNIPAQUE injection according to the specific dosing tables [see Dosage and Administration (2.2, 2.3, 2.4, 2.5, 2.6, 2.7, 2.8, 2.9)]. Consider factors such as age, body weight, vessel size, blood flow rate within the vessel, anticipated pathology, degree and extent of opacification required, structures or area to be examined, disease processes affecting the patient, and equipment and technique to be employed.
- Hydrate patients before and after administration of OMNIPAQUE injection [see Warnings and Precautions (5.4)].
- Use aseptic technique for all handling and administration of OMNIPAQUE injection.
- Administer OMNIPAQUE injection at either body (37°C, 98.6°F) or room temperature (20°C to 25°C, 68°F to 77°F).
- Do not mix OMNIPAQUE injection with, or inject in intravenous lines containing, other drugs or total nutritional admixtures except when OMNIPAQUE injection is administered in an automated contrast injection system or contrast management system suitable for simultaneous injection of OMNIPAQUE injection and 0.9% Sodium Chloride Injection [see Dosage and Administration (2.10, 2.11)].
- Parenteral drug products should be inspected visually for particulate matter and discoloration prior to administration, whenever solution and container permit.
- Each container of OMNIPAQUE injection and OMNIPAQUE oral solution in single-dose containers are intended for one procedure only. Discard any unused portion.

2.2 Recommended Dosage for Intrathecal Procedures in Adults

- The recommended doses for intrathecal procedures in adults are shown in Table 1.
- Administer over 1 minute to 2 minutes.
- If sequential or repeat examinations are required, allow at least 48 hours for clearance of the drug from the body before repeat administration; however, whenever possible, 5 days to 7 days is recommended.
- If CT myelography is performed, delay imaging by several hours to reduce the degree of contrast.

Table 1. Recommended Concentrations and Volumes of OMNIPAQUE Injection for Intrathecal Procedures in Adults
Imaging Procedure | Injection Type | Concentration (mg Iodine/mL) | Volume to Administer
Lumbar Myelography | Lumbar | 180 [Use single-dose containers or 500 mL Pharmacy Bulk Packages [see Dosage and Administration (2.11)].] | 10 mL to 17 mL
Lumbar Myelography | Lumbar | 240 | 7 mL to 12.5 mL
Thoracic Myelography | Lumbar Cervical | 240 | 6 mL to 12.5 mL
Thoracic Myelography | Lumbar Cervical | 300 | 6 mL to 10 mL
Cervical Myelography | Lumbar | 240 | 6 mL to 12.5 mL
Cervical Myelography | Lumbar | 300 | 6 mL to 10 mL
Cervical Myelography | C1-2 | 180 | 7 mL to 10 mL
Cervical Myelography | C1-2 | 240 | 6 mL to 12.5 mL
Cervical Myelography | C1-2 | 300 | 4 mL to 10 mL
Total Columnar Myelography | Lumbar | 240 | 6 mL to 12.5 mL
Total Columnar Myelography | Lumbar | 300 | 6 mL to 10 mL
CT Cisternography | Lumbar | 180 | 10 mL to 17 mL
CT Cisternography | Lumbar | 240 | 7 mL to 12.5 mL

2.3 Recommended Dosage for Intra-arterial Procedures in Adults

The recommended doses for intra-arterial procedures in adults are shown in Table 2.

Table 2. Recommended Concentrations and Volumes of OMNIPAQUE Injection for Intra-arterial Procedures in Adults
Imaging Procedure |  | Concentration (mg Iodine/mL) | Volume to Administer per Single Injection for Selective Injection Sites | Maximum Cumulative Total Dose
Cardiac Ventriculography |  | 350 [Use single-dose containers or a 500 mL Pharmacy Bulk Package [see Dosage and Administration (2.11)].] | 40 mL (Range of 30 mL to 60 mL) may be combined with selective coronary arteriography | 250 mL
Aortography and Selective Visceral Arteriography |  | 300 | - Aorta (aortic arch, ascending aorta): 50 mL to 80 mL - Abdominal aorta and its branches (celiac, mesenteric, hepatic, and splenic arteries): 30 mL to 60 mL - Renal arteries: 5 mL to 15 mL | 290 mL
Aortography and Selective Visceral Arteriography |  | 350 | - Aorta (aortic arch, ascending aorta): 50 mL to 80 mL - Abdominal aorta and its branches (celiac, mesenteric, hepatic, and splenic arteries): 30 mL to 60 mL - Renal arteries: 5 mL to 15 mL | 250 mL
Aortic root and arch study when used alone |  | 350 | 50 mL (Range of 20 mL to 75 mL) | 250 mL
Selective Coronary Arteriography |  | 350 | 5 mL (Range of 3 mL to 14 mL) | 250 mL
Cerebral Arteriography |  | 300 | - Common carotid artery: 6 mL to 12 mL - Internal carotid artery: 8 mL to 10 mL - External carotid artery: 6 mL to 9 mL - Vertebral artery: 6 mL to 10 mL | 290 mL
Peripheral Arteriography | Aortofemoral Runoffs | 300 | 30 mL to 90 mL | 290 mL
Peripheral Arteriography | Aortofemoral Runoffs | 350 | 20 mL to 70 mL | 250 mL
Peripheral Arteriography | Selective Arteriogram | 300 | 10 mL to 60 mL | 290 mL
Peripheral Arteriography | Selective Arteriogram | 350 | 10 mL to 30 mL | 250 mL
IA-DSA (head, neck, abdominal, renal, and peripheral vessels) |  | 140 | - Aorta: 20 mL to 45 mL at 8 mL/sec to 20 mL/sec - Carotid artery: 5 mL to 10 mL at 3 mL/sec to 6 mL/sec - Femoral artery: 9 mL to 20 mL at 3 mL/sec to 6 mL/sec - Vertebral artery: 4 mL to 10 mL at 2 mL/sec to 8 mL/sec - Renal arteries: 6 mL to 12 mL at 3 mL/sec to 6 mL/sec - Other branches of aorta (includes subclavian, axillary, innominate, and iliac): 8 mL to 25 mL at 3 mL/sec to 10 mL/sec | 250 mL

2.4 Recommended Dosage for Intravenous Procedures in Adults

The recommended doses for intravenous procedures in adults are shown in Table 3.

Table 3. Recommended Concentrations and Volumes of OMNIPAQUE Injection for Intravenous Procedures in Adults
Imaging Procedure |  | Concentration (mg Iodine/mL) | Volume to Administer
Excretory Urography |  | 300 [Use single-dose containers or 500 mL Pharmacy Bulk Packages [see Dosage and Administration (2.11)].] | 0.6 mL/kg to 1.2 mL/kg body weight (maximum dose is 102 mL)
Excretory Urography |  | 350 | 0.6 mL/kg to 1.2 mL/kg body weight (maximum dose is 102 mL)
CT | Head | 240 | 120 mL to 250 mL by infusion
CT | Head | 300 [Use single-dose containers, 500 mL Imaging Bulk Packages or Pharmacy Bulk Packages, or 150 mL single-dose bottles with an automated contrast injection system or contrast management system [see Dosage and Administration (2.10, 2.11, 2.12)].] | 70 mL to 150 mL by rapid injection
CT | Head | 350 | 80 mL by rapid injection
CT | Body | 300 | 50 mL to 200 mL by rapid injection
CT | Body | 350 | 60 mL to 100 mL by rapid injection
Peripheral Venography (phlebography) |  | 240 | 20 mL to 150 mL per leg
Peripheral Venography (phlebography) |  | 300 | 40 mL to 100 mL per leg
IV-DSA (head, neck, abdominal, renal, and peripheral vessels) |  | 350 | 30 mL to 50 mL at 7.5 mL/sec to 30 mL/sec using a pressure injector Frequently three or more doses may be required; the maximum cumulative total dose is 250 mL

2.5 Recommended Dosage for Oral Procedures in Adults

Recommended Dosage for Radiographic Examination of the GI Tract in Adults

The recommended dose for radiographic examination of the GI tract in adults is 50 mL to 100 mL of OMNIPAQUE injection 350 mg iodine/mL administered undiluted orally.

Recommended Dosage for CT of the Abdomen and Pelvis in Conjunction with Intravenous Administration of OMINIPAQUE Injection in Adults

The recommended oral dose using diluted OMNIPAQUE injection or OMNIPAQUE oral solution and concurrent intravenous doses for CT of the abdomen and pelvis in adults are shown in Table 4.

Table 4. Recommended Concentrations and Volumes of Diluted OMNIPAQUE Injection or OMNIPAQUE Oral Solution for Oral Administration and Concurrent Intravenous OMNIPAQUE Injection for CT of the Abdomen and Pelvis in Adults
Concentration (mg Iodine/mL) | Volume to Administer | Administration Instructions
Oral Dose Using Diluted OMNIPAQUE Injection
6 mg Iodine/mL to 12 mg Iodine/mL of Diluted OMNIPAQUE Injection [See Table 5 for dilution instructions of OMNIPAQUE injection] | 500 mL to 1,000 mL | - Administer the oral dose all at once or over a period of up to 45 minutes if there is difficulty in consuming the required volume. - Use a higher iodine concentration of the diluted product if a smaller volume needs to be administered (see Table 5).
Oral Dose Using OMNIPAQUE Oral Solution
9 mg Iodine/mL or 12 mg Iodine/mL of OMNIPAQUE Oral Solution | 500 mL to 1,000 mL | Administer the oral dose all at once or over a period of up to 45 minutes if there is difficulty in consuming the required volume.
Intravenous Dose of OMNIPAQUE injection in Conjunction with Oral Administration
300 [Use single-dose containers, 500 mL Imaging or Pharmacy Bulk Packages, or 150 mL single-dose bottles with an automated contrast injection system or contrast management system [see Dosage and Administration (2.10, 2.11, 2.12)].] | 100 mL to 150 mL | Administer up to 40 minutes AFTER consumption of the oral dose.

Preparation of Diluted OMNIPAQUE Injection for Oral Administration for CT of the Abdomen and Pelvis in Adults

- Prepare the diluted OMNIPAQUE injection in water, carbonated beverage, milk, infant formula, or juice just prior to administration according to Table 5.
- Discard any unused portion after the procedure.

Table 5. Volumes of OMNIPAQUE Injection and Added Liquid to Dilute OMNIPAQUE Injection for Oral Administration for CT of the Abdomen in Adults
Concentration of Diluted OMNIPAQUE injection (mg iodine/mL) | Dilution Method 1 |  | Dilution Method 2 |  | Dilution Method 3
Concentration of Diluted OMNIPAQUE injection (mg iodine/mL) | Volume of OMNIPAQUE 240 mg Iodine/mL (mL) | Volume of Added Liquid [Use water, carbonated beverage, milk, infant formula, or juice.] (mL) | Volume of OMNIPAQUE 300 mg Iodine/mL (mL) | Volume of Added Liquid (mL) | Volume of OMNIPAQUE 350 mg Iodine/mL (mL) | Volume of Added Liquid (mL)
6 | 25 | 975 | 20 | 980 | 17 | 983
9 | 38 | 962 | 30 | 970 | 26 | 974
12 | 50 | 950 | 40 | 960 | 35 | 965
15 | 63 | 937 | 50 | 950 | 43 | 957
18 | 75 | 925 | 60 | 940 | 52 | 948
21 | 88 | 912 | 70 | 930 | 60 | 940

2.6 Recommended Dosage for Intraarticular Procedures in Adults

- The recommended doses for intraarticular procedures in adults are shown in Table 6.
- Use passive or active manipulation to disperse the medium throughout the joint space.

Table 6. Recommended Concentrations and Volumes of OMNIPAQUE Injection for Intraarticular Procedures in Adults
Imaging Procedure | Location | Concentration (mg Iodine/mL) | Volume to Administer | Double Contrast/Single Contrast
Arthrography | Knee | 240 [Use single-dose containers or 500 mL Pharmacy Bulk Packages [see Dosage and Administration (2.11)].] | 5 mL to 15 mL | Lower volumes recommended for double-contrast examinations; higher volumes recommended for single-contrast examinations.
Arthrography | Knee | 300 | 5 mL to 15 mL | Lower volumes recommended for double-contrast examinations; higher volumes recommended for single-contrast examinations.
Arthrography | Knee | 350 | 5 mL to 10 mL | Lower volumes recommended for double-contrast examinations; higher volumes recommended for single-contrast examinations.
Arthrography | Shoulder | 300 | 10 mL | Lower volumes recommended for double-contrast examinations; higher volumes recommended for single-contrast examinations.
Arthrography | Temporomandibular | 300 | 0.5 mL to 1 mL | Lower volumes recommended for double-contrast examinations; higher volumes recommended for single-contrast examinations.

2.7 Recommended Dosage for Body Cavity Procedures in Adults

- The recommended doses for body cavity procedures in adults are shown in Table 7.
- Volume to administer may vary depending on individual anatomy and/or disease state.

Table 7. Recommended Concentrations and Volumes of OMNIPAQUE Injection for Body Cavity Procedures in Adults
Imaging Procedure | Concentration (mg Iodine/mL) | Volume to Administer | Route of Administration
Endoscopic retrograde pancreatography (ERP) and cholangiopancreatography (ERCP) | 240 [Use single-dose containers or 500 mL Pharmacy Bulk Packages [see Dosage and Administration (2.11)].] | 10 mL to 50 mL | Intraductal
Herniography | 240 | 15 mL to 20 mL | Intraperitoneal
Herniography | 300 | 15 mL to 20 mL | Intraperitoneal
Hysterosalpingography | 240 | 50 mL | Intrauterine

2.8 Recommended Dosage for Intrathecal, Intra-arterial, and Intravenous Procedures in Pediatric Patients

Recommended Dosage for Intrathecal Procedures in Pediatric Patients Aged 2 Weeks and Older

- Recommended doses based on age for intrathecal procedures in pediatric patients aged 2 weeks and older are shown in Table 8.
- Administer over 1 minute to 2 minutes.
- If sequential or repeat examinations are required, allow at least 48 hours for clearance of the drug from the body before repeat administration; however, whenever possible, 5 days to 7 days is recommended.
- If CT myelography is performed, delay imaging by several hours to reduce the degree of contrast.

Table 8: Recommended Concentrations and Volumes of OMNIPAQUE Injection Based on Age for Intrathecal Procedure in Pediatric Patients Aged 2 Weeks and Older
Imaging Procedure | Injection Type | Age | Concentration (mg Iodine/mL) | Volume to Administer
- Myelography - Lumbar - Thoracic - Cervical - Total Columnar - CT cisternography | Lumbar | 2 weeks up to 3 months | 180 [Use single-dose containers.] | 2 mL to 4 mL
- Myelography - Lumbar - Thoracic - Cervical - Total Columnar - CT cisternography | Lumbar | 3 months up to 36 months | 180 [Use single-dose containers.] | 4 mL to 8 mL
- Myelography - Lumbar - Thoracic - Cervical - Total Columnar - CT cisternography | Lumbar | 3 years up to 7 years | 180 [Use single-dose containers.] | 5 mL to 10 mL
- Myelography - Lumbar - Thoracic - Cervical - Total Columnar - CT cisternography | Lumbar | 7 years up to 13 years | 180 [Use single-dose containers.] | 5 mL to 12 mL
- Myelography - Lumbar - Thoracic - Cervical - Total Columnar - CT cisternography | Lumbar | 13 years to 18 years | 180 [Use single-dose containers.] | 6 mL to 15 mL

Recommended Dosage for Intra-arterial Procedures in Pediatric Patients

The recommended doses for intra-arterial procedures in pediatric patients are shown in Table 9.

Table 9. Recommended Concentrations and Volumes of OMNIPAQUE Injection per Body Weight for Intra-arterial Procedures in Pediatric Patients
Imaging Procedure | Concentration (mg Iodine/mL) | Volume per Body Weight to Administer per Single Injection | Maximum Cumulative Volume
Cardiac Ventriculography | 300 [Use single-dose containers or 500 mL Pharmacy Bulk Packages [see Dosage and Administration (2.11)].] | 1.75 mL/kg (Range of 1.5 mL/kg to 2 mL/kg) | 6 mL/kg up to a total volume of 290 mL
Cardiac Ventriculography | 350 | 1.25 mL/kg (Range of 1 mL/kg to 1.5 mL/kg) | 5 mL/kg up to a total volume of 250 mL
Aortography (aortic root, aortic arch, and descending aorta) | 350 | 1 mL/kg | 5 mL/kg up to a total volume of 250 mL
Pulmonary Angiography | 350 | 1 mL/kg | 5 mL/kg up to a total volume of 250 mL

Recommended Dosage for Intravenous Procedures in Pediatric Patients

The recommended doses for intravenous procedures in pediatric patients are shown in Table 10.

Table 10. Recommended Concentrations and Volumes of OMNIPAQUE Injection per Body Weight for Intravenous Procedures in Pediatric Patients
Imaging Procedure | Concentration (mg Iodine/mL) | Volume per Body Weight to Administer
Excretory Urography | 300 [Use single-dose containers or 500 mL Pharmacy Bulk Packages [see Dosage and Administration (2.11)].] | 0.5 mL/kg to 3 mL/kg (Maximum single dose: 116 mL)
CT of the Head and Body | 240 | 1 mL/kg to 2 mL/kg (with maximum 3 mL/kg) (Maximum single dose: 116 mL)
CT of the Head and Body | 300 [Use single-dose containers, 500 mL Imaging or Pharmacy Bulk Packages, or 150 mL single-dose bottles with an automated contrast injection system or contrast management system [see Dosage and Administration (2.10, 2.11, 2.12)].] | 1 mL/kg to 2 mL/kg (with maximum 3 mL/kg) (Maximum single dose: 116 mL)

2.9 Recommended Dosage for Oral or Rectal and Body Cavity Procedures in Pediatric Patients

Recommended Dosage for Radiographic Examination of the GI Tract in Pediatric Patients

- The recommended doses for radiographic examination of the GI tract are shown in Table 11.
- Administer orally or rectally.

Table 11. Recommended Concentrations and Volumes of OMNIPAQUE Injection Based on Age for Radiographic Examination of the GI Tract in Pediatric Patients
Age | Concentration (mg iodine/mL) | Oral Volume | Rectal Volume
Less than 3 months | 180 [Use single-dose containers or 500 mL Pharmacy Bulk Packages [see Dosage and Administration (2.11)].] | 5 mL to 30 mL | May be a larger volume than the volume given orally (up to 300 mL)
3 months to 3 years | 180, 240, or 300 | Up to 60 mL | May be a larger volume than the volume given orally (up to 300 mL)
4 years to 10 years | 180, 240, or 300 | Up to 80 mL | May be a larger volume than the volume given orally (up to 300 mL)
Greater than 10 years | 180, 240, or 300 | Up to 100 mL | May be a larger volume than the volume given orally (up to 300 mL)

Recommended Dosage for CT of the Abdomen and Pelvis in Conjunction with Intravenous Administration of OMNIPAQUE in Pediatric Patients

The recommended oral dose using diluted OMNIPAQUE injection or OMNIPAQUE oral solution and concurrent intravenous dose for CT of the abdomen and pelvis in pediatric patients are shown in Table 12.

Table 12. Recommended Concentrations and Volumes of Diluted OMNIPAQUE Injection or OMNIPAQUE Oral Solution for Oral Administration and Concurrent Intravenous OMNIPAQUE Injection for CT of the Abdomen and Pelvis in Pediatric Patients
Concentration (mg Iodine/mL) | Volume to Administer | Administration Instructions | Maximum Dose by Age or Body Weight
Oral Dose Using Diluted OMNIPAQUE Injection
9 mg Iodine/mL to 21 mg Iodine/mL of Diluted OMNIPAQUE Injection [See Table 13 for dilution instructions of OMNIPAQUE injection] | 180 mL to 750 mL | - Administer the oral dose all at once or over a period of up to 45 minutes if there is difficulty in consuming the required volume. - Use a higher iodine concentration of the diluted product if a smaller volume needs to be administered (see Table 13). | - less than 3 years old: 5 grams iodine - 3 years old to 18 years old: 10 grams iodine
Oral Dose Using OMNIPAQUE Oral Solution
6 mg Iodine/mL or 12 mg Iodine/mL of OMNIPAQUE Oral Solution | 180 mL to 750 mL | Administer the oral dose all at once or over a period of up to 45 minutes if there is difficulty in consuming the required volume. | - less than 3 years old: 5 grams iodine - 3 years old to 18 years old: 10 grams iodine
Intravenous Dose in Conjunction with Oral Administration
240 or 300 [Use single-dose containers, 500 mL Imaging or Pharmacy Bulk Packages, or 150 mL single-dose bottles with an automated contrast injection system or contrast management system [see Dosage and Administration (2.10, 2.11, 2.12)].] | 2 mL/kg body weight (with a range of 1 mL/kg to 2 mL/kg) | Administer up to 60 minutes AFTER consumption of the oral dose. | 3 mL/kg (maximum single dose: 116 mL)

Preparation of Diluted OMNIPAQUE Injection for Oral Administration for CT of the Abdomen and Pelvis in Pediatric Patients

- Prepare the diluted OMNIPAQUE injection in water, carbonated beverage, milk, infant formula, or juice just prior to administration according to Table 13.
- Discard any unused portion after the procedure.

Table 13. Volumes of OMNIPAQUE Injection and Added Liquid to Dilute OMNIPAQUE Injection for Oral Administration for CT of the Abdomen and Pelvis in Pediatric Patients
Concentration of Diluted OMNIPAQUE injection (mg iodine/mL) | Dilution Method 1 |  | Dilution Method 2 |  | Dilution Method 3
Concentration of Diluted OMNIPAQUE injection (mg iodine/mL) | Volume of OMNIPAQUE 240 mg iodine/mL (mL) | Volume of Added Liquid [Use water, carbonated beverage, milk, infant formula, or juice.] (mL) | Volume of OMNIPAQUE 300 mg Iodine/mL (mL) | Volume of Added Liquid (mL) | Volume of OMNIPAQUE 350 mg Iodine/mL (mL) | Volume of Added Liquid (mL)
6 | 25 | 975 | 20 | 980 | 17 | 983
9 | 38 | 962 | 30 | 970 | 26 | 974
12 | 50 | 950 | 40 | 960 | 35 | 965
15 | 63 | 937 | 50 | 950 | 43 | 957
18 | 75 | 925 | 60 | 940 | 52 | 948
21 | 88 | 912 | 70 | 930 | 60 | 940

Recommended Dosage for Voiding Cystourethrography in Pediatric Patients

- Voiding cystourethrography (VCU) can be performed in conjunction with excretory urography [see Dosage and Administration (2.8)].
- The concentration of diluted OMNIPAQUE injection may vary depending upon the patient's size and age and with the technique and equipment used.
- Volume ranges of diluted OMNIPAQUE injection 50 mg iodine/mL and 100 mg iodine/mL are shown in Table 14.
- Dilute OMNIPAQUE injection with Sterile Water for Injection according to Table 15, utilizing aseptic technique, just prior to use.
- Discard any unused portion after the procedure.

Table 14. Volume Ranges of Diluted OMNIPAQUE Injection for VCU in Pediatric Patients
Concentration of Diluted OMNIPAQUE Injection [See Table 15 below for dilution instructions of OMNIPAQUE injection.] (mg iodine/mL) | Volume to Administer
50 | 50 mL to 600 mL by intravesical administration
100 | 50 mL to 300 mL by intravesical administration

Table 15. Volumes of OMNIPAQUE Injection and Sterile Water for Injection to Dilute OMNIPAQUE Injection for VCU in Pediatric Patients
Concentration of Diluted OMNIPAQUE injection (mg iodine/mL) | Dilution Method 1 |  | Dilution Method 2 |  | Dilution Method 3
Concentration of Diluted OMNIPAQUE injection (mg iodine/mL) | Volume of OMNIPAQUE 240 mg Iodine/mL (mL) | Volume of Sterile Water for Injection (mL) | Volume of OMNIPAQUE 300 mg Iodine/mL (mL) | Volume of Sterile Water for Injection (mL) | Volume of OMNIPAQUE 350 mg Iodine/mL (mL) | Volume of Sterile Water for Injection (mL)
50 | 100 | 380 | 100 | 500 | 100 | 600
60 | 100 | 300 | 100 | 400 | 100 | 483
70 | 100 | 243 | 100 | 330 | 100 | 400
80 | 100 | 200 | 100 | 275 | 100 | 338
90 | 100 | 167 | 100 | 233 | 100 | 289
100 | 100 | 140 | 100 | 200 | 100 | 250

2.10 Directions for Use of the 500 mL Bottles of OMNIPAQUE Injection 300 mg Iodine/mL and 350 mg Iodine/mL as Imaging Bulk Package

- OMNIPAQUE injection 300 mg iodine/mL and OMNIPAQUE injection 350 mg iodine/mL in 500 mL bottles may be used as an Imaging Bulk Package (IBP) for intravenous use [see Dosage and Administration (2.4, 2.8)].
- When used as an IBP, check the appropriate box on the container label to indicate that the selected container is to be utilized as an Imaging Bulk Package. This container is for use only with an automated contrast injection system, contrast management system, or contrast media transfer set approved or cleared for use with this contrast agent in this IBP. See device labeling for information on devices indicated for use with this IBP and techniques to help assure safe use.
- Use the OMNIPAQUE IBP and 0.9% Sodium Chloride Injection USP in a room designated for radiological procedures that involve administration of a contrast agent.
- Using aseptic technique, penetrate the container closure only one time with a suitable sterile component of the automated contrast injection system, contrast management system, or contrast media transfer set cleared for use with the OMNIPAQUE IBP.
- If 0.9% Sodium Chloride Injection USP is used with the OMNIPAQUE IBP, prepare the 0.9% Sodium Chloride Injection USP sterile port in accordance with the dosage and administration section of its approved prescribing information and affix the saline tag provided with the OMNIPAQUE IBP on the 0.9% Sodium Chloride Injection USP container.
- Once the OMNIPAQUE IBP and 0.9% Sodium Chloride Injection containers are punctured, do not remove them from the work area during the entire period of use. Maintain the OMNIPAQUE IBP in an inverted position such that container contents are in continuous contact with the dispensing set.
- After the container closure is punctured, if the integrity of the OMNIPAQUE IBP, the 0.9% Sodium Chloride Injection, and the delivery system cannot be assured through direct continuous supervision, discard the IBP, 0.9% Sodium Chloride Injection USP, and all associated disposables for the contrast media transfer set.
- A maximum time from initial puncture is 8 hours. Discard any unused portion.

2.11 Directions for Use of the 500 mL Bottles of OMNIPAQUE Injection 300 mg Iodine/mL and 350 mg Iodine/mL as Pharmacy Bulk Package

- OMNIPAQUE injection 300 mg iodine/mL and OMNIPAQUE injection 350 mg iodine/mL in 500 mL bottles contain many single doses and may be used as a Pharmacy Bulk Package (PBP).
- When used as a PBP, check the appropriate box on the container label to indicate that the selected container is to be utilized as a Pharmacy Bulk Package. This container is not for direct infusion; it is for use in pharmacy admixture service to dispense aliquots using a suitable dispensing set under a laminar flow hood or equivalent clean air compounding area using aseptic technique.
- Penetrate the container closure only one time, utilizing a suitable transfer device and aseptic technique.
- The withdrawal of container contents should be accomplished without delay. However, should this not be possible, a maximum time of 8 hours from initial closure entry is permitted to complete fluid transfer operations.
- Do not remove the container from the aseptic area during the entire 8-hour period.
- The temperature of the container should not exceed 37°C (98.6°F), after the closure has been entered.
- Discard any unused portion after 8 hours from the initial closure entry.

2.12 Directions for Use of the 150 mL Bottles of OMNIPAQUE Injection 300 mg Iodine/mL and 350 mg Iodine/mL with an Automated Contrast Injection System or Contrast Management System

- OMNIPAQUE injection 300 mg iodine/mL and OMNIPAQUE injection 350 mg iodine/mL in 150 mL bottles may be used with a contrast media management system cleared for use with OMNIPAQUE injection 300 mg iodine/mL and 350 mg iodine/mL in 150 mL bottles.
- See device labeling for information on device indications, instructions for use, and techniques to help assure safe use.
- Using aseptic technique, penetrate the container closure only one time with a suitable sterile component of the contrast media management system cleared for use with OMNIPAQUE 300 mg iodine/mL and 350 mg iodine/mL in 150 mL bottles.
- Once the container is punctured, do not remove the bottle from the work area during the entire period of use.
- Maximum use time is 4 hours after initial puncture.
- Each bottle is for one procedure only. Discard unused portion.

3 DOSAGE FORMS AND STRENGTHS

Injection and Oral Solution: Colorless to pale yellow solution available in the following presentations:

Dosage Form | Concentration (mg of iodine/mL) | Package Size | Package Type
Injection | 140 | 50 mL | Single-Dose Bottle
Injection | 180 | 10 mL | Single-Dose Vial
Injection | 240 | 10 mL and 20 mL | Single-Dose Vial
Injection | 240 | 50 mL and 100 mL | Sigle-Dose Bottle
Injection | 300 | 10 mL | Single-Dose Vial
Injection | 300 | 30 mL, 50 mL, 100 mL, 125 mL, and 150 mL | Single-Dose Bottle
Injection | 300 | 500 mL [OMNIPAQUE injection 300 mg iodine/mL and OMNIPAQUE injection 350 mg iodine/mL in bottles of 500 mL can be used as either an Imaging Bulk Package or a Pharmacy Bulk Package [see Dosage and Administration (2.10, 2.11)].] | Imaging or Pharmacy Bulk Package
Injection | 350 | 50 mL, 75 mL, 100 mL, 125 mL, 150 mL, and 200 mL | Single-Dose Bottle
Injection | 350 | 500 mL | Imaging or Pharmacy Bulk Package
Oral Solution | 9 | 500 mL | Single-Dose Bottle
Oral Solution | 12 | 500 mL | Single-Dose Bottle

4 CONTRAINDICATIONS

OMNIPAQUE for hysterosalpingography is contraindicated during pregnancy or suspected pregnancy, menstruation or when menstruation is imminent, within 6 months after termination of pregnancy, within 30 days after conization or curettage, when signs of infection are present in any portion of the genital tract including the external genitalia, and when reproductive tract neoplasia is known or suspected because of the risk of peritoneal spread of neoplasm.

5 WARNINGS AND PRECAUTIONS

5.1 Risks Associated with Intrathecal Administration of OMNIPAQUE Injection 140 mg Iodine/mL and 350 mg Iodine/mL

Use only the iodine concentrations and presentations recommended for intrathecal procedures [see Dosage and Administration (2.2, 2.8)]. Intrathecal administration of OMNIPAQUE of a wrong iodine concentration, even if inadvertent, can cause death, convulsions, seizures, cerebral hemorrhage, coma, paralysis, arachnoiditis, acute renal failure, cardiac arrest, rhabdomyolysis, hyperthermia, and brain edema.

5.2 Risks Associated with Parenteral Administration of OMNIPAQUE Oral Solution

Adverse reactions such as hemolysis may occur if OMNIPAQUE oral solution is administered intravenously or intraarterially due to low osmolality [see Description (11)]. OMNIPAQUE oral solution is for oral use only.

5.3 Hypersensitivity Reactions

OMNIPAQUE can cause life-threatening or fatal hypersensitivity reactions including anaphylaxis. Manifestations include respiratory arrest, laryngospasm, bronchospasm, angioedema, and shock. Most severe reactions develop shortly after the start of the injection (within 1 to 3 minutes), but delayed reactions can also occur. There is an increased risk in patients with a history of a previous reaction to contrast agent and known allergic disorders (i.e., bronchial asthma, drug, or food allergies) or other hypersensitivities. Premedication with antihistamines or corticosteroids does not prevent serious life-threatening reactions but may reduce both their incidence and severity.

Obtain a history of allergy, hypersensitivity, or hypersensitivity reactions to iodinated contrast agents and always have emergency resuscitation equipment and trained personnel available prior to OMNIPAQUE administration. Monitor all patients for hypersensitivity reactions.

5.4 Acute Kidney Injury

Acute kidney injury, including renal failure, may occur after parenteral administration of OMNIPAQUE. Risk factors include: pre-existing renal impairment, dehydration, diabetes mellitus, congestive heart failure, advanced vascular disease, elderly age, concomitant use of nephrotoxic or diuretic medications, multiple myeloma/paraproteinaceous diseases, repetitive and/or large doses of an iodinated contrast agent.

Use the lowest necessary dose of OMNIPAQUE in patients with renal impairment. Adequately hydrate patients prior to and following parenteral administration of OMNIPAQUE. Do not use laxatives, diuretics, or preparatory dehydration prior to OMNIPAQUE administration.

5.5 Cardiovascular Adverse Reactions

Life-threatening or fatal cardiovascular reactions including hypotension, shock, cardiac arrest have occurred with the parenteral administration of OMNIPAQUE. Most deaths occur during injection or five to ten minutes later, with cardiovascular disease as the main aggravating factor. Cardiac decompensation, serious arrhythmias, and myocardial ischemia or infarction can occur during coronary arteriography and ventriculography.

Based on clinical literature, reported deaths from the administration of iodinated contrast agents range from 6.6 per million (0.00066%) to 1 in 10,000 (0.01%). Use the lowest necessary dose of OMNIPAQUE in patients with congestive heart failure and always have emergency resuscitation equipment and trained personnel available. Monitor all patients for severe cardiovascular reactions.

5.6 Thromboembolic Events

Serious, rarely fatal, thromboembolic events causing myocardial infarction and stroke can occur during angiocardiography procedures with iodinated contrast agents including OMNIPAQUE. During these procedures, increased thrombosis and activation of the complement system occurs. Risk factors for thromboembolic events include: length of procedure, catheter and syringe material, underlying disease state, and concomitant medications.

To minimize thromboembolic events, use meticulous angiographic techniques, and minimize the length of the procedure. Avoid blood remaining in contact with syringes containing OMNIPAQUE, which increases the risk of clotting. Avoid angiocardiography in patients with homocystinuria because of the risk of inducing thrombosis and embolism.

5.7 Extravasation and Injection Site Reactions

Extravasation of OMNIPAQUE during intravenous or intra-arterial injection may cause tissue necrosis and/or compartment syndrome, particularly in patients with severe arterial or venous disease. Ensure intravenous or intra-arterial placement of catheters prior to injection. Monitor patients for extravasation and advise patients to seek medical care for progression of symptoms.

5.8 Thyroid Storm in Patients with Hyperthyroidism

Thyroid storm has occurred after the intravenous or intra-arterial use of iodinated contrast agents in patients with hyperthyroidism, or with an autonomously functioning thyroid nodule. Evaluate the risk in such patients before use of OMNIPAQUE.

5.9 Thyroid Dysfunction in Pediatric Patients 0 to 3 Years of Age

Thyroid dysfunction characterized by hypothyroidism or transient thyroid suppression has been reported after both single exposure and multiple exposures to iodinated contrast media (ICM) in pediatric patients 0 to 3 years of age.

Younger age, very low birth weight, prematurity, underlying medical conditions affecting thyroid function, admission to neonatal or pediatric intensive care units, and congenital cardiac conditions are associated with an increased risk of hypothyroidism after ICM exposure. Pediatric patients with congenital cardiac conditions may be at the greatest risk given that they often require high doses of contrast during invasive cardiac procedures.

An underactive thyroid during early life may be harmful for cognitive and neurological development and may require thyroid hormone replacement therapy. After exposure to ICM, individualize thyroid function monitoring based on underlying risk factors, especially in term and preterm neonates.

5.10 Hypertensive Crisis in Patients with Pheochromocytoma

Hypertensive crisis has occurred after the use of iodinated contrast agents in patient with pheochromocytoma. Monitor patients when administering OMNIPAQUE intravenously or intra-arterially if pheochromocytoma or catecholamine-secreting paragangliomas are suspected. Inject the minimum amount of contrast necessary, assess the blood pressure throughout the procedure, and have measures for treatment of a hypertensive crisis readily available.

5.11 Sickle Cell Crisis in Patients with Sickle Cell Disease

Iodinated contrast agents when administered intravenously or intra-arterially may promote sickling in individuals who are homozygous for sickle cell disease. Hydrate patients prior to and following OMNIPAQUE administration and use OMNIPAQUE only if the necessary imaging information cannot be obtained with alternative imaging modalities.

5.12 Severe Cutaneous Adverse Reactions

Severe cutaneous adverse reactions (SCAR) may develop from 1 hour to several weeks after intravenous or intra-arterial contrast agent administration. These reactions include Stevens-Johnson syndrome and toxic epidermal necrolysis (SJS/TEN), acute generalized exanthematous pustulosis (AGEP) and drug reaction with eosinophilia and systemic symptoms (DRESS). Reaction severity may increase and time to onset may decrease with repeat administration of contrast agents; prophylactic medications may not prevent or mitigate severe cutaneous adverse reactions. Avoid administering OMNIPAQUE to patients with a history of a severe cutaneous adverse reaction to OMNIPAQUE.

5.13 Interference with Laboratory Test

OMNIPAQUE can interfere with protein-bound iodine test [see Drug Interactions (7.2)].

5.14 Increased Risk of Seizures with Intrathecal Procedures

Focal and generalized motor seizures have been reported after intrathecal use of iodinated contrast agents. In several of the cases, higher than recommended doses were administered.

Use of medications that may lower the seizure threshold (phenothiazine derivatives, including those used for their antihistaminic properties; tricyclic antidepressants; MAO inhibitors; CNS stimulants; analeptics; antipsychotic agents) should be carefully evaluated. Consider discontinuing these agents at least 48 hours before and for at least 24 hours following intrathecal administration of OMNIPAQUE.

6 ADVERSE REACTIONS

The following clinically significant adverse reactions are described elsewhere in the labeling:

- Risks Associated with Intrathecal Administration of OMNIPAQUE Injection 140 mg Iodine/mL and 350 mg Iodine/mL [see Warnings and Precautions (5.1)]
- Risks Associated with Parenteral Administration of OMNIPAQUE Oral Solution [see Warnings and Precautions (5.2)]
- Hypersensitivity Reactions [see Warnings and Precautions (5.3)]
- Acute Kidney Injury [see Warnings and Precautions (5.4)]
- Cardiovascular Adverse Reactions [see Warnings and Precautions (5.5)]
- Thromboembolic Events [see Warnings and Precautions (5.6)]
- Thyroid Dysfunction in Pediatric Patients 0 to 3 Years of Age [see Warnings and Precautions (5.9)]
- Severe Cutaneous Adverse Reactions [see Warnings and Precautions (5.12)]

6.1 Clinical Trials Experience

Because clinical trials are conducted under widely varying conditions, adverse reaction rates observed in the clinical trials of a drug cannot be directly compared to rates in the clinical trials of another drug and may not reflect the rates observed in practice.

Intrathecal Administration

Adults

Adverse reactions (≥1%) in 1,531 adult patients following intrathecal administration of OMNIPAQUE in clinical trials are presented in Table 16.

Table 16. Adverse Reactions (≥1%) in in Adult Patients Following Intrathecal Administration of OMNIPAQUE in Clinical Trials
System Organ Class | Adverse Reaction | Incidence N=1,531
Nervous system disorders | Headaches | 18%
Musculoskeletal and connective tissue disorders | Pain including backache, neckache, stiffness, neuralgia | 8%
Gastrointestinal disorders | Nausea | 6%
Gastrointestinal disorders | Vomiting | 3%
Nervous System disorders | Dizziness | 2%

Other adverse reactions (<1%) were:

Ear and labyrinth disorders: tinnitus, vertigo

Eye disorders: photophobia

General disorders and administration site conditions: sensation of heat

Metabolism and nutrition disorders: loss of appetite

Musculoskeletal and connective tissue disorders: feeling of heaviness

Nervous system disorders: drowsiness, hypertonia, neuralgia, neurological changes, paresthesia, syncope

Renal and urinary disorders: difficulty in micturition

Skin and subcutaneous tissue disorders: sweating

Vascular disorders: hypertension, hypotension

Pediatric Patients

The adverse reactions reported in pediatric patients following intrathecal administration of OMNIPAQUE were generally similar to those reported in adults. A total of 152 pediatric patients were administered OMNIPAQUE 180 mg iodine/mL intrathecally by lumbar puncture for pediatric myelography in clinical trials. Adverse reactions (≥1%) are presented in Table 17.

Table 17. Adverse Reactions (≥1%) in Pediatric Patients Following Intrathecal Administration of OMNIPAQUE 180 mg iodine/mL by Lumbar Puncture for Myelography in Clinical Trials
System Organ Class | Adverse Reaction | Incidence N=152
Nervous system disorders | Headache | 9%
Gastrointestinal disorders | Vomiting | 6%
Musculoskeletal and connective tissue disorders | Backache | 1.3%

Other adverse reactions (<1%) were:

Gastrointestinal disorders: stomachache

General disorders and administration site conditions: fever

Nervous system disorders: neurological changes

Psychiatric disorders: visual hallucination

Skin and subcutaneous tissue disorders: hives

Intra-arterial or Intravenous Administration

Adults

Adverse reactions (≥1%) in 1,485 adult patients following intra-arterial or intravenous administration of OMNIPAQUE in clinical trials are presented in Table 18.

Table 18. Adverse Reactions (≥1%) in Adult Patients Following Intra-arterial or Intravenous Administration of OMNIPAQUE in Clinical Trials
System Organ Class | Adverse Reaction | Incidence (N=1,485)
Cardiac disorders | Arrhythmias including PVCs and PACs | 2%
Nervous system disorders | Pain | 3%
Nervous system disorders | Vision abnormalities including blurred vision and photomas | 2%
Nervous system disorders | Taste perversion | 1%
Gastrointestinal disorders | Nausea | 2%

Other adverse reactions (<1%) were:

Cardiac disorders: hypotension, cardiac failure, asystole, bradycardia, tachycardia, vasovagal reaction

Respiratory, thoracic and mediastinal disorders: dyspnea, rhinitis, coughing, laryngitis

Gastrointestinal disorders: vomiting, diarrhea, dyspepsia, cramp, dry mouth

General disorders and administration site conditions: fever, shivering

Nervous system disorders: cerebral infarction, convulsion, hemiparesis, motor and speech dysfunction, nystagmus, paresthesia, somnolence, transient ischemic attack, vertigo including dizziness and lightheadedness

Musculoskeletal and connective tissue disorders: still neck

Skin and subcutaneous tissue disorders: urticaria, abscess, pruritus, purpura

Psychiatric disorders: anxiety, syncope

Pediatric Patients

Adverse reactions reported in pediatric patients following intra-arterial or intravenous administration of OMNIPAQUE were generally similar in quality and frequency to those reported in adults. A total of 391 pediatric patients in clinical trials were administered OMNIPAQUE 240 mg iodine/mL, 300 mg iodine/mL, or 350 mg iodine/mL by intra-arterial or intravenous injection for pediatric cardiac ventriculography, excretory urography, and CT head imaging.

Adverse reactions (≥1%) were vomiting (2%) and nausea (1%).

Other adverse reactions (<1%) were:

Cardiac disorders: Ventricular tachycardia, 2:1 heart block, hypertension, anemia

General disorders and administration site conditions: Pain, fever

Nervous system disorders: Convulsion, taste abnormality

Respiratory, thoracic and mediastinal disorders: Congestion, apnea

Endocrine disorders: Hypoglycemia

Skin and subcutaneous tissue disorders: Rash

Oral or Rectal Administration for Examination of the Gastrointestinal Tract

Adults

A total of 54 adult patients were administered undiluted OMNIPAQUE 350 mg iodine/mL by oral route for radiographic examination of the gastrointestinal tract in clinical trials. Adverse reactions (≥1%) are presented in Table 19.

Table 19. Adverse Reactions (≥1%) in Adult Patients Following Oral Administration of Undiluted OMNIPAQUE 350 mg Iodine/mL in Clinical Trials
System Organ Class | Adverse Reaction | Incidence N=54
Gastrointestinal disorders | Diarrhea | 42%
Gastrointestinal disorders | Nausea | 15%
Gastrointestinal disorders | Vomiting | 11%
Gastrointestinal disorders | Abdominal Pain | 7%
Gastrointestinal disorders | Flatulence | 2%
Nervous system disorders | Headache | 2%

Pediatrics Patients

A total of 58 pediatric patients were administered OMNIPAQUE by oral or rectal administration in clinical trials. Adverse reactions (≥1%) are presented in Table 20.

Table 20. Adverse Reactions (≥1%) in Pediatric Patients Following Oral or Rectal Administration of OMNIPAQUE in Clinical Trials
System Organ Class | Adverse Reaction | Incidence N=58
Gastrointestinal disorders | Diarrhea | 36%
Gastrointestinal disorders | Vomiting | 9%
Gastrointestinal disorders | Nausea | 5%
Gastrointestinal disorders | Abdominal pain | 2%
General disorders and administration site conditions | Fever | 5%
Skin and subcutaneous tissue disorders | Urticaria | 2%
Vascular disorders | Hypotension | 2%

Oral Administration for CT of the Abdomen in Conjunction with Intravenous Administration

Adults

A total of 44 adult patients received diluted OMNIPAQUE (4-9 mg iodine/mL) by oral route in conjunction with intravenously injected OMNIPAQUE 300 mg iodine/mL for CT examination of the abdomen in clinical trials. Adverse reactions (≥1%) were limited to a single report of vomiting (2.3%).

Pediatric Patients

A total of 69 pediatric patients received diluted OMNIPAQUE (9-29 mg iodine/mL) by oral route in conjunction with intravenously administered OMNIPAQUE 240 mg iodine/mL or OMNIPAQUE 300 mg iodine/mL for CT examination of the abdomen in clinical trials. Adverse reactions (≥1%) were limited to a single report of vomiting (1.4%).

Intraarticular Administration

Arthrography in Adults

A total of 285 adult patients received OMNIPAQUE 240 mg iodine/mL, 300 mg iodine/mL, or 350 mg iodine/mL for various body cavity examinations in clinical trials. The most frequent adverse reactions (≥1%) were administration site pain (26%) and swelling (22%) in arthrography. Patients also experienced heat (7%).

Body Cavity Use

VCU in Pediatric Patients

No new adverse reactions associated with the use of OMNIPAQUE for VCU procedures were reported in 51 pediatric patients studied.

6.2 Post-marketing Experience

The following adverse reactions have been identified during post-approval use of OMNIPAQUE. Because these reactions are reported voluntarily from a population of uncertain size, it is not always possible to reliably estimate their frequency or establish a causal relationship to drug exposure.

General

Immune system disorders: Hypersensitivity reactions, anaphylactic or anaphylactoid reactions, anaphylactic or anaphylactoid shock including life-threatening or fatal anaphylaxis

General disorders and administration site conditions: Pyrexia, chills, pain and discomfort, asthenia, administration site conditions including extravasation

Intrathecal Administration

Nervous system disorders: Meningism, aseptic meningitis, seizures or status epilepticus, disorientation, coma, depressed or loss of consciousness, transient contrast-induced toxic encephalopathy (including amnesia, hallucination, paralysis, paresis, speech disorder, aphasia, dysarthria), restlessness, tremors, hypoesthesia

Musculoskeletal and connective tissue disorders: Pain, muscle spasms or spasticity

Psychiatric disorders: Confusional state, agitation, anxiety

Eye disorders: Transient visual impairment including cortical blindness

Renal and urinary disorders: Acute kidney injury

Intra-arterial or Intravenous Administration

Cardiac disorders: Severe cardiac complications (including cardiac arrest, cardiopulmonary arrest), shock, peripheral vasodilatation, palpitations, vasospasm including spasm of coronary arteries, myocardial infarction, syncope, cyanosis, pallor, flushing, chest pain

Vascular disorders: Vasospasm and thrombophlebitis following intravenous injection

Blood and lymphatic system disorders: Neutropenia

Nervous system disorders: Disorientation, coma, depressed or loss of consciousness, transient contrast-induced toxic encephalopathy (including amnesia, hallucination, paralysis, paresis, speech disorder, aphasia, dysarthria), restlessness, tremors, hypoesthesia

Psychiatric disorders: Confusional state, agitation

Eye disorders: Eye irritation or itchiness, periorbital edema, ocular or conjunctival hyperemia, lacrimation

Renal and urinary disorders: Acute kidney injury, toxic nephropathy (CIN), transient proteinuria, oliguria or anuria, increased serum creatinine

Gastrointestinal disorders: Abdominal pain, pancreatitis aggravated, salivary gland enlargement

Endocrine disorders: Hyperthyroidism, hypothyroidism

Respiratory, thoracic and mediastinal disorders: Respiratory distress, respiratory failure, pulmonary edema, bronchospasm, laryngospasm, throat irritation, throat tightness, laryngeal edema, wheezing, chest discomfort, asthmatic attack

Skin and subcutaneous tissue disorders: Contrast media reactions range from mild (e.g., pleomorphic rashes, drug eruption, erythema and skin discoloration, blisters, hyperhidrosis, angioedema, localized areas of edema) to severe (e.g., Stevens-Johnson syndrome and toxic epidermal necrolysis [SJS/TEN], bullous or exfoliative dermatitis, acute generalized exanthematous pustulosis [AGEP] and drug reaction with eosinophilia and systemic symptoms [DRESS])

Oral Administration

Gastrointestinal disorders: Dysphagia, abdominal pain

Body Cavity Administration

Gastrointestinal disorders: Pancreatitis

Musculoskeletal and connective tissue disorders: Arthritis (arthrography)

Hysterosalpingography: Injection of OMNIPAQUE for hysterosalpingography is associated with immediate, transient pain. Monitor injection pressure and volume instilled to minimize pain and to avoid disruptive distention of the uterus and fallopian tubes. Fluoroscopic monitoring is recommended.

Nervous system disorders: Pain (49%), somnolence and fever each with an individual incidence of 3%

Gastrointestinal disorders: Nausea (3%)

7 DRUG INTERACTIONS

7.1 Drug-Drug Interactions

Metformin

In patients with renal impairment, metformin can cause lactic acidosis. Iodinated contrast agents appear to increase the risk of metformin-induced lactic acidosis, possibly as a result of worsening renal function. Stop metformin at the time of, or prior to, OMNIPAQUE administration in patients with an eGFR between 30 and 60 mL/min/1.73 m^2; in patients with a history of hepatic impairment, alcoholism or heart failure; or in patients who will be administered intra-arterial iodinated contrast. Re-evaluate eGFR 48 hours after the imaging procedure, and reinstitute metformin only after renal function is stable.

Radioactive Iodine

OMNIPAQUE may interfere with thyroid uptake of radioactive iodine (I-131 and I-123) and decrease therapeutic and diagnostic efficacy. Avoid thyroid therapy or testing for up to 6 weeks post OMNIPAQUE.

7.2 Drug-Laboratory Test Interactions

Protein-Bound Iodine Test

Iodinated contrast agents, including OMNIPAQUE, will temporarily increase protein-bound iodine in blood. Do not perform protein-bound iodine test for at least 16 days following administration of OMNIPAQUE. However, thyroid function tests that do not depend on iodine estimation, e.g., T3 resin uptake or direct thyroxine assays, are not affected.

8 USE IN SPECIFIC POPULATIONS

8.1 Pregnancy

Risk Summary

Hysterosalpingography is contraindicated in pregnant women due to the potential risk to the fetus from an intrauterine procedure [see Contraindications (4)]. There are no data with iohexol use in pregnant women to inform any drug-associated risks. Iohexol crosses the placenta and reaches fetal tissues in small amounts (see Data). In animal reproduction studies, no developmental toxicity occurred with intravenous iohexol administration to rats and rabbits at doses up to 0.4 (rat) and 0.5 (rabbit) times the maximum recommended human intravenous dose (see Data).

The estimated background risk of major birth defects and miscarriage for the indicated population is unknown. All pregnancies have a background risk of birth defect, loss or other adverse outcomes. In the U.S. general population, the estimated background risk of major birth defects and miscarriage in clinically recognized pregnancies is 2 to 4% and 15 to 20%, respectively.

Data

Human Data

Literature reports show that intravenously administered iohexol crosses the placenta and is visualized in the digestive tract of exposed infants after birth.

Animal Data

Iohexol was neither embryotoxic nor teratogenic in either rats or rabbits at the following dose levels tested: 1.0, 2.0, 4.0 g iodine/kg in rats, administered intravenously to 3 groups of 25 dams once daily during days 6 through 15 of pregnancy; 0.3, 1.0, 2.5 g iodine/kg in rabbits, administered intravenously to 3 groups of 18 rabbits dosed once a day during days 6 through 18 of pregnancy.

8.2 Lactation

Risk Summary

Published literature reports that breast feeding after intravenous iohexol administration to the mother would result in the infant receiving an oral dose of approximately 0.7% of the maternal intravenous dose; however, lactation studies have not been conducted with oral, intrathecal, or intracavity administration of iohexol. There is no information on the effects of the drug on the breastfed infant or on milk production. Iodinated contrast agents are excreted unchanged in human milk in very low amounts with poor absorption from the gastrointestinal tract of a breastfed infant. Exposure to iohexol to a breastfed infant can be minimized by temporary discontinuation of breastfeeding (see Clinical Considerations). The developmental and health benefits of breastfeeding should be considered along with the mother's clinical need for OMNIPAQUE and any potential adverse effects on the breastfed infant from OMNIPAQUE or from the underlying maternal condition.

Clinical Considerations

Interruption of breastfeeding after exposure to iodinated contrast agents is not necessary because the potential exposure of the breastfed infant to iodine is small. However, a lactating woman may consider interrupting breastfeeding and pumping and discarding breast milk for 10 hours (approximately 5 elimination half-lives) after OMNIPAQUE administration to minimize drug exposure to a breastfed infant.

8.4 Pediatric Use

Intrathecal Use

The safety and effectiveness of OMNIPAQUE have been established in pediatric patients aged 2 weeks and older for myelography and CT myelography (lumbar, thoracic, cervical, total columnar) and for CT cisternography. Use of OMNIPAQUE is supported by controlled clinical studies in adults for myelography, in addition to clinical studies in pediatric patients undergoing myelography.

The safety and effectiveness of OMNIPAQUE have not been established for intrathecal use in pediatric patients less than 2 weeks of age.

The safety and effectiveness of OMNIPAQUE for CT cerebral ventriculography have not been established in pediatric patients.

Intra-arterial or Intravenous Use

Cardiac Ventriculography, Aortography, and Pulmonary Angiography

The safety and effectiveness of OMNIPAQUE have been established in pediatric patients from birth to 17 years of age for cardiac ventriculography, aortography, and pulmonary angiography. Use of OMNIPAQUE is supported by controlled clinical studies in adults for cardiac ventriculography and aortography, in addition to controlled clinical studies in pediatric patients undergoing cardiac ventriculography, including aortography.

Excretory Urography

The safety and effectiveness of OMNIPQUE have been established in pediatric patients from birth to 17 years of age for excretory urography. Use of OMNIPAQUE is supported by controlled clinical studies in adults for urography, in addition to controlled clinical studies in pediatric patients undergoing urography and clinical safety data in pediatric patients down to birth.

CT of the Head and Body

The safety and effectiveness of OMNIPAQUE have been established in pediatric patients from birth to 17 years of age for CT imaging of the head and body. Use of OMNIPAQUE is supported by controlled clinical studies in adults for head and body CT, in addition to clinical studies in pediatric patients undergoing head CT and in 69 pediatric patients undergoing CT of the abdomen after oral administration of diluted OMNIPAQUE plus intravenous administration of OMNIPAQUE.

Selective Coronary Arteriography, Cerebral and Peripheral Arteriography, Intra-arterial Digital Subtraction Angiography, Peripheral Venography, and Intravenous Digital Subtraction Angiography

The safety and effectiveness of OMNIPAQUE have not been established in pediatric patients for selective coronary arteriography, cerebral or peripheral arteriography, intra-arterial digital subtraction angiography, peripheral venography, and intravenous digital subtraction angiography.

Oral or Rectal Use

Examination of the GI Tract

The safety and effectiveness of OMNIPAQUE have been established in pediatric patients, from birth to 17 years of age for examination of the GI tract. Use of OMNIPAQUE is supported by controlled studies in adults for examination of the GI tract, in addition to clinical studies in pediatric patients undergoing examination of the GI tract.

CT of the Abdomen and Pelvis in Conjunction with Intravenous Use

The safety and effectiveness of OMNIPAQUE for CT of the abdomen and pelvis have been established in pediatric patients from birth to 17 years of age. Use is supported by clinical trials in adults, in addition to clinical studies in 69 pediatric patients undergoing CT of the abdomen.

Intraarticular Use

The safety and effectiveness of OMNIPAQUE have not been established in pediatric patients for arthrography.

Body Cavity Use

Voiding Cystourethrography

OMNIPAQUE is indicated for use in pediatric patients from birth to 17 years of age for voiding cystourethrography (VCU). Use for voiding cystourethrography is supported by clinical studies in 51 pediatric patients undergoing VCU.

ERCP, Herniography, and Hysterosalpingography

The safety and effectiveness of OMNIPAQUE have not been established in pediatric patients for ERCP, herniography, or hysterosalpingography.

In general, the frequency of adverse reactions in pediatric patients was similar to that seen in adults [see Adverse Reactions (6.1)]. Pediatric patients at higher risk of experiencing adverse events during contrast-medium administration may include those having asthma, a sensitivity to medication and/or allergens, congestive heart failure, a serum creatinine greater than 1.5 mg/dL or those less than 12 months of age.

Thyroid function tests indicative of thyroid dysfunction, characterized by hypothyroidism or transient thyroid suppression have been reported following iodinated contrast media administration in pediatric patients, including term and preterm neonates. Some patients were treated for hypothyroidism. After exposure to iodinated contrast media, individualize thyroid function monitoring in pediatric patients 0 to 3 years of age based on underlying risk factors, especially in term and preterm neonates [see Warnings and Precautions (5.9) and Adverse Reactions (6.2)].

8.5 Geriatric Use

In clinical studies of OMNIPAQUE for CT of the head and body, 52 (17%) of patients were 70 and over. No overall differences in safety were observed between these patients and younger patients. Other reported clinical experience has not identified differences in safety and effectiveness between the elderly and younger patients.

Iohexol is substantially excreted by the kidney, and the risk of adverse reactions to iohexol may be greater in patients with impaired renal function. Because elderly patients are more likely to have decreased renal function, care should be taken in dose selection, and it may be useful to monitor renal function.

8.6 Renal Impairment

The clearance of iohexol decreases with increasing degree of renal impairment and results in delayed opacification of the urinary system. In addition, preexisting renal impairment increases the risk for acute kidney injury [see Warnings and Precautions (5.4)]. Iohexol can be removed by dialysis.

10 OVERDOSAGE

The adverse effects of overdosage in intra-arterial or intravenous administration are life-threatening and affect mainly the pulmonary and cardiovascular systems. The symptoms include: cyanosis, bradycardia, acidosis, pulmonary hemorrhage, convulsions, coma, and cardiac arrest. Treatment of an overdosage is directed toward the support of all vital functions, and prompt institution of symptomatic therapy. Iohexol can be dialyzed.

11 DESCRIPTION

Iohexol is a nonionic radiographic contrast agent available as:

- OMNIPAQUE (iohexol) injection for intrathecal, intra-arterial, intravenous, oral, rectal, intraarticular, and body cavity use
- OMNIPAQUE (iohexol) oral solution for oral use

The chemical name of iohexol is Bis(2,3-dihydroxypropyl)-5-[N-(2,3-dihydroxypropyl)-acetamido]-2,4,6- triiodoisophthalamide with a molecular weight of 821.14 (iodine content 46.36%). Iohexol has the following structural formula:

OMNIPAQUE injection is a sterile, pyrogen-free, colorless to pale yellow solution available in five concentrations of iodine:

- OMNIPAQUE 140 mg iodine/mL: Each mL contains 302 mg iohexol (providing 140 mg organically bound iodine) and the following inactive ingredients: 0.1 mg edetate calcium disodium and 1.21 mg tromethamine.
- OMNIPAQUE 180 mg iodine/mL: Each mL contains 388 mg iohexol (providing 180 mg organically bound iodine) and the following inactive ingredients: 0.1 mg edetate calcium disodium and 1.21 mg tromethamine.
- OMNIPAQUE 240 mg iodine/mL: Each mL contains 518 mg iohexol (providing 240 mg organically bound iodine) and the following inactive ingredients: 0.1 mg edetate calcium disodium and 1.21 mg tromethamine.
- OMNIPAQUE 300 mg iodine/mL: Each mL contains 647 mg iohexol (providing 300 mg organically bound iodine) and the following inactive ingredients: 0.1 mg edetate calcium disodium and 1.21 mg tromethamine.
- OMNIPAQUE 350 mg iodine/mL: Each mL contains 755 mg iohexol (providing 350 mg organically bound iodine) and the following inactive ingredients: 0.1 mg edetate calcium disodium and 1.21 mg tromethamine.

OMNIPAQUE oral solution is a sterile, pyrogen-free, colorless to pale yellow solution available in two concentrations of iodine:

- OMNIPAQUE oral solution 9 mg iodine/mL: Each mL contains 19 mg iohexol (providing 9 mg organically bound iodine) and the following inactive ingredients: 0.1 mg edetate calcium disodium and 1.21 mg tromethamine.
- OMNIPAQUE oral solution 12 mg iodine/mL: Each mL contains 26 mg iohexol (providing 12 mg organically bound iodine) and the following inactive ingredients: 0.1 mg edetate calcium disodium and 1.21 mg tromethamine.

The pH is adjusted between 6.8 and 7.7 with hydrochloric acid or sodium hydroxide. OMNIPAQUE injection and OMNIPAQUE oral solution contain no preservatives and no ingredient made from a gluten-containing grain (wheat, barley, or rye).

OMNIPAQUE injection and OMNIPAQUE oral solution have the following physical properties:

Table 21. Physicochemical Properties of OMNIPAQUE
Dosage Form | Concentration (mg iodine/mL) | Osmolality [By vapor-pressure osmometry.] (mOsmol/kg water) | Absolute Viscosity (cP) |  | Specific Gravity
Dosage Form | Concentration (mg iodine/mL) | Osmolality [By vapor-pressure osmometry.] (mOsmol/kg water) | 20°C | 37°C | 37°C
Injection | 140 | 322 | 2.3 | 1.5 | 1.164
Injection | 180 | 408 | 3.1 | 2.0 | 1.209
Injection | 240 | 520 | 5.8 | 3.4 | 1.280
Injection | 300 | 672 | 11.8 | 6.3 | 1.349
Injection | 350 | 844 | 20.4 | 10.4 | 1.406
Oral solution | 9 | 38 | 1.1 | 0.8 | 1.011
Oral solution | 12 | 45 | 1.1 | 0.8 | 1.014

OMNIPAQUE injection has osmolalities from approximately 1.1 to 3 times that of plasma (285 mOsmol/kg water) or cerebrospinal fluid (301 mOsmol/kg water) as shown in the above table and are hypertonic .

OMNIPAQUE oral solution is hypotonic.

12 CLINICAL PHARMACOLOGY

12.1 Mechanism of Action

The iodine atoms in iohexol provide attenuation of X-rays in direct proportion to the concentration of iohexol. Since concentration changes over time, iohexol provides time-dependent image contrast which may assist in visualizing body structures.

12.2 Pharmacodynamics

Intrathecal Administration

The initial concentration and volume of the contrast medium, in conjunction with patient manipulation and the volume of cerebrospinal fluid (CSF) into which the contrast medium is placed, will determine the extent of the contrast that can be achieved. Following intrathecal injection in conventional radiography, OMNIPAQUE 180 mg iodine/mL, 240 mg iodine/mL, and 300 mg iodine/mL will continue to provide contrast for at least 30 minutes. Slow diffusion of iohexol takes place throughout the CSF with subsequent absorption into the bloodstream. At approximately 1 hour following injection, contrast will no longer be sufficient for conventional myelography.

After administration into the lumbar subarachnoid space, computerized tomography shows the presence of contrast medium in the thoracic region in about 1 hour, in the cervical region in about 2 hours, and in the basal cisterns in 3 to 4 hours.

Intravenous or Intra-arterial Administration

Following intravenous or intra-arterial administration of OMNIPAQUE, the degree of contrast enhancement is directly related to the iodine concentration of an administered dose; peak iodine blood concentrations occur immediately (15 seconds to 120 seconds) following rapid intravenous injection. The time to maximum contrast enhancement can vary, depending on the organ, from the time that peak blood iodine concentrations are reached to one hour after intravenous bolus administration. When a delay between peak blood iodine concentrations and peak contrast is present, it suggests that radiographic contrast enhancement is at least in part dependent on the accumulation of iodine containing agent within the lesion and outside the blood pool.

Oral Administration

Orally administered OMNIPAQUE produces visualization of the gastrointestinal tract. Less than 1% of orally administered iohexol is recovered in the urine, suggesting minimal amounts are absorbed from the normal gastrointestinal tract. This amount may increase in the presence of bowel perforation or bowel obstruction.

Intraarticular Administration

Visualization of the joint spaces can be accomplished by direct injection of contrast medium. For intraarticular cavities, the injected iohexol is absorbed into the surrounding tissue and subsequently absorbed into systemic circulation.

Body Cavity Administration

For most body cavities, the injected iohexol is absorbed into the surrounding tissue and subsequently absorbed into systemic circulation. Examinations of the uterus (hysterosalpingography) and bladder (voiding cystourethrography) involve the almost immediate drainage of contrast medium from the cavity upon conclusion of the radiographic procedure.

12.3 Pharmacokinetics

Following the intravenous administration of iohexol (between 500 mg iodine/kg to 1,500 mg iodine/kg) to 16 adult subjects, apparent first-order terminal elimination half-life was 12.6 hours and total body clearance was 131 (98 to 165) mL/min. Clearance was not dose dependent.

Absorption

As evidenced by the amount recovered in urine, <1% of orally administered iohexol is absorbed from the normal gastrointestinal tract. This amount may increase in the presence of bowel perforation or bowel obstruction.

Distribution

In 16 adult subjects (receiving between 500 mg iodine/kg to 1,500 mg iodine/kg intravenous iohexol) the plasma volume of distribution was165 (108 to 219) mL/kg.

In five adult patients receiving 16 mL to 18 mL of OMNIPAQUE (180 mg iodine/mL) by lumbar intrathecal injection the plasma volume of distribution was 559 (350 to 849) mL/kg.

Elimination

Metabolism

No significant metabolism, deiodination or biotransformation occurs.

Excretion

Following intravenous, intra-arterial or intrathecal administration, iohexol is excreted unchanged by glomerular filtration. Approximately 90% of the intravenously injected iohexol dose is excreted within the first 24 hours. Following intravenous or intraarterial administration, peak urine concentration occurs in the first hour after injection.

13 NONCLINICAL TOXICOLOGY

13.1 Carcinogenesis, Mutagenesis, Impairment of Fertility

Long-term animal studies have not been performed with iohexol to evaluate carcinogenic potential. Iohexol was not genotoxic in a series of studies, including the Ames test, the mouse lymphoma TK locus forward mutation assay, and a mouse micronucleus assay. Iohexol did not impair the fertility of male or female rats when repeatedly administered at intravenous dosages up to 4 g iodine/kg.

14 CLINICAL STUDIES

The safety and effectiveness of OMNIPAQUE for CT of the head were evaluated in three clinical studies. Each study also used an ionic high-osmolar iodinated contrast agent as a comparator. A total of 280 patients were randomized to administration of either OMNIPAQUE (n=142) or the comparator (n=138). OMNIPAQUE patients had a mean age of 52 years (range 16 to 85), 41% were women, and were administered a mean of 692 mg iodine/kg (range 337 to 1,250 mg iodine/kg) by intravenous injection with OMNIPAQUE 240 mg iodine/mL (1 study) or 300 mg iodine/mL (2 studies).

Efficacy was determined from investigator ratings of quality of contrast enhancement (none, poor, good, or excellent; only scans rated as good or excellent were considered diagnostic).

The percentage of OMNIPAQUE-enhanced scans rated as good or excellent was 100% in the two studies using OMNIPAQUE 300 mg iodine/mL, and 79% in the third study using OMNIPAQUE 240 mg iodine/mL.

16 HOW SUPPLIED/STORAGE AND HANDLING

How Supplied

OMNIPAQUE (iohexol) injection and OMNIPAQUE (iohexol) oral solution are colorless to pale yellow solutions available in the following presentations:

Dosage Form | Concentration (mg iodine/mL) | Package Size | Package Type & Material | Sale Unit | NDC
Injection | 140 | 50 mL | Single-Dose Polymer Bottles | Boxes of 10 | 0407-1401-52
Injection | 180 | 10 mL | Single-Dose Glass Vials | Boxes of 10 | 0407-1411-10
Injection | 240 | 10 mL | Single-Dose Glass Vials | Boxes of 10 | 0407-1412-10
Injection | 240 | 20 mL | Single-Dose Glass Vials | Boxes of 10 | 0407-1412-20
Injection | 240 | 50 mL | Single-Dose Polymer Bottles | Boxes of 10 | 0407-1412-30
Injection | 240 | 100 mL | Single-Dose Polymer Bottles | Boxes of 10 | 0407-1412-33
Injection | 300 | 10 mL | Single-Dose Glass Vials | Boxes of 10 | 0407-1413-10
Injection | 300 | 30 mL | Single-Dose Polymer Bottles | Boxes of 10 | 0407-1413-59
Injection | 300 | 50 mL | Single-Dose Polymer Bottles | Boxes of 10 | 0407-1413-61
Injection | 300 | 100 mL | Single-Dose Polymer Bottles | Boxes of 10 | 0407-1413-63
Injection | 300 | 125 mL | Single-Dose Glass Bottles | Boxes of 10 | 0407-1413-53
Injection | 300 | 150 mL | Single-Dose Polymer Bottles | Boxes of 10 | 0407-1413-65
Injection | 300 | 500 mL [OMNIPAQUE injection 300 mg iodine/mL and OMNIPAQUE injection 350 mg iodine/mL in bottles of 500 mL can be used as either an Imaging Bulk Package or a Pharmacy Bulk Package [see Dosage and Administration (2.10, 2.11)].] | Imaging or Pharmacy Bulk Package Polymer Bottles | Boxes of 10 | 0407-1413-72
Injection | 350 | 50 mL | Single-Dose Polymer Bottles | Boxes of 10 | 0407-1414-89
Injection | 350 | 75 mL | Single-Dose Polymer Bottles | Boxes of 10 | 0407-1414-90
Injection | 350 | 100 mL | Single-Dose Polymer Bottles | Boxes of 10 | 0407-1414-91
Injection | 350 | 125 mL | Single-Dose Glass Bottles | Boxes of 10 | 0407-1414-76
Injection | 350 | 150 mL | Single-Dose Polymer Bottles | Boxes of 10 | 0407-1414-93
Injection | 350 | 200 mL | Single-Dose Polymer Bottles | Boxes of 10 | 0407-1414-94
Injection | 350 | 500 mL | Imaging or Pharmacy Bulk Package Polymer Bottles | Boxes of 10 | 0407-1414-72
Oral Solution | 9 | 500 mL | Single-Dose Polymer Bottles | Boxes of 10 | 0407-1415-09
Oral Solution | 12 | 500 mL | Single-Dose Polymer Bottles | Boxes of 10 | 0407-1416-12

The container closure system components (bottle, vial, stopper, and cap) of OMNIPAQUE injection and OMNIPAQUE oral solution are not made with natural rubber latex.

Storage and Handling

- OMNIPAQUE Injection: Store at 20°C to 25°C (68°F to 77°F); excursions permitted to 15°C to 30°C (59°F to 86°F) [see USP Controlled Room Temperature]. May be stored in a contrast media warmer for up to one month, not to exceed 37°C (98.6°F).
- OMNIPAQUE Oral Solution: Store between 0°C and 30°C (32°F to 86°F).

Protect from light. Do not freeze. Discard any product that is inadvertently frozen, as freezing may compromise the closure integrity of the immediate container.

17 PATIENT COUNSELING INFORMATION

Hypersensitivity Reactions

Advise the patient concerning the risk of hypersensitivity reactions that can occur both during and after OMNIPAQUE administration. Advise the patient to report any signs or symptoms of hypersensitivity reactions during the procedure and to seek immediate medical attention for any signs or symptoms experienced after discharge [see Warnings and Precautions (5.3)].

Advise patients to inform their physician if they develop a rash after receiving OMNIPAQUE [see Warnings and Precautions (5.12)].

Acute Kidney Injury

Advise the patient concerning appropriate hydration to decrease the risk of contrast-induced acute kidney injury [see Warnings and Precautions (5.4)].

Extravasation

If extravasation occurs during injection, advise patients to seek medical care for progression of symptoms [see Warnings and Precautions (5.7)].

Lactation

Advise a lactating woman that interruption of breastfeeding is not necessary. However, to avoid any exposure, a lactating woman may consider pumping and discarding breast milk for 10 hours after OMNIPAQUE administration [see Use in Specific Populations (8.2)].

Thyroid Dysfunction

Advise parents/caregivers about the risk of developing thyroid dysfunction after OMNIPAQUE administration. Advise parents/caregivers about when to seek medical care for their child to monitor for thyroid function [see Warnings and Precautions (5.9)].

Distributed by GE Healthcare Inc., Marlborough, MA 01752 U.S.A.

OMNIPAQUE is a trademark of GE HealthCare or one of its subsidiaries.
GE is a trademark of General Electric Company used under trademark license.

© 2024 GE HealthCare

PRINCIPAL DISPLAY PANEL - 300 mg Bottle Box Label

GE Healthcare

Y-538I

Contains
10 x 500 mL
Bottles

NDC 0407-1413-72

OMNIPAQUE™
(iohexol) Injection

300 mg Iodine/mL

This container can be used either as:

IMAGING BULK PACKAGE
For Intravenous Use Only

or

PHARMACY BULK PACKAGE
Not for Direct Infusion
For Intrathecal, Intra-arterial,
Intravenous, Oral, Rectal,
Intraarticular, or Body Cavity Use

Rx ONLY
See prescribing information for dosage and administration.

Store at 20°C to 25°C (68°F to 77°F); excursions permitted to 15°C to 30°C
(59°F to 86°F) [see USP Controlled Room Temperature]. May be stored in a
contrast media warmer for up to one month, not to exceed 37°C (98.6°F).
Protect from light. Do not freeze. Discard unused OMNIPAQUE 8 hours
after initial puncture.

Each mL contains 647 mg of iohexol (300 mg organically bound iodine),
0.1 mg edetate calcium disodium, and 1.21 mg tromethamine.
The pH is adjusted between 6.8 and 7.7 with hydrochloric acid or sodium
hydroxide. No preservative added.

+PLUSPAK™ (polymer bottle)

Distributed by GE Healthcare Inc.,
Marlborough, MA 01752 U.S.A.
For inquiries call 1-800-654-0118

Exp.: DD MMM YYYY
Lot: 12345678

0000000 USA

PRINCIPAL DISPLAY PANEL - 350 mg Bottle Box Label

GE Healthcare

Y-548I

Contains
10 x 500 mL
Bottles

NDC 0407-1414-72

OMNIPAQUE™
(iohexol) Injection

350 mg Iodine/mL

This container can be used either as:

IMAGING BULK PACKAGE
For Intravenous Use Only

or

PHARMACY BULK PACKAGE
Not for Direct Infusion

For Intra-arterial,
Intravenous, Oral, Rectal,
Intraarticular, or Body Cavity Use

NOT FOR INTRATHECAL USE

Rx ONLY
See prescribing information for dosage and administration.

Store at 20°C to 25°C (68°F to 77°F); excursions permitted to 15°C to 30°C
(59°F to 86°F) [see USP Controlled Room Temperature]. May be stored in a
contrast media warmer for up to one month, not to exceed 37°C (98.6°F).
Protect from light. Do not freeze. Discard unused OMNIPAQUE 8 hours
after initial puncture.

Each mL contains 755 mg of iohexol (350 mg organically bound iodine),
0.1 mg edetate calcium disodium, and 1.21 mg tromethamine.
The pH is adjusted between 6.8 and 7.7 with hydrochloric acid or sodium
hydroxide. No preservative added.

+PLUSPAK™ (polymer bottle)

Distributed by GE Healthcare Inc.,
Marlborough, MA 01752 U.S.A.
For inquiries call 1-800-654-0118

Exp.: DD MMM YYYY
Lot: 12345678

0000000 USA